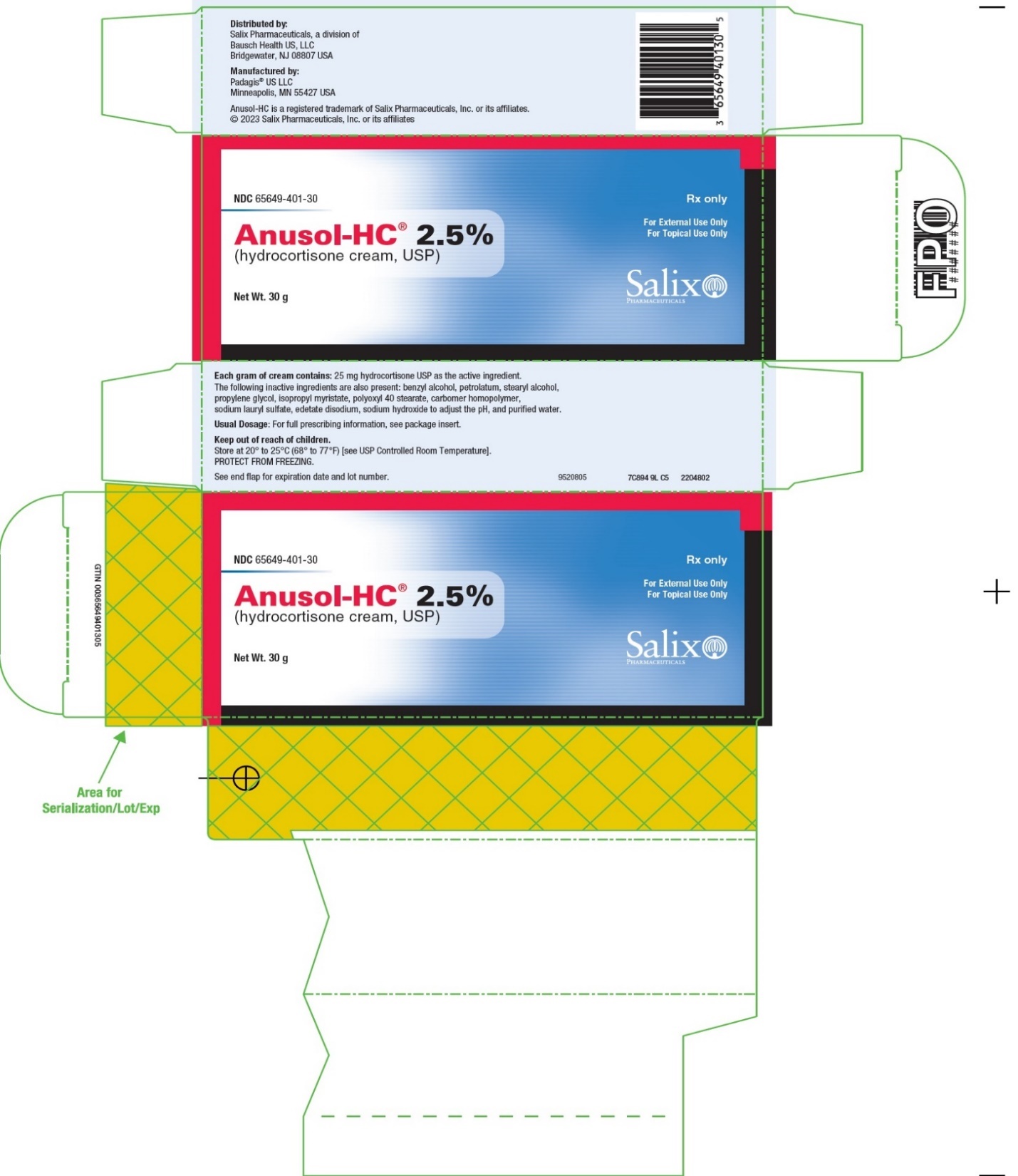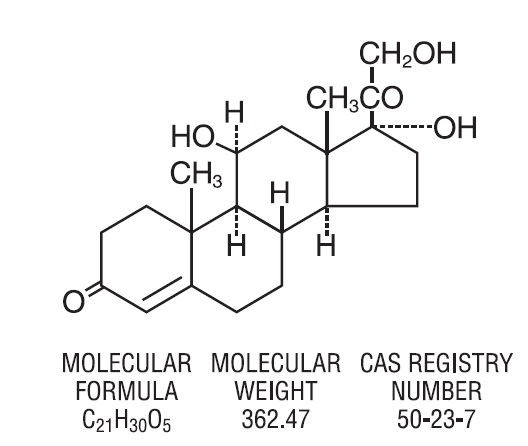 DRUG LABEL: Anusol
NDC: 65649-401 | Form: CREAM
Manufacturer: Salix Pharmaceuticals, Inc
Category: prescription | Type: HUMAN PRESCRIPTION DRUG LABEL
Date: 20230601

ACTIVE INGREDIENTS: HYDROCORTISONE 25 mg/1 g
INACTIVE INGREDIENTS: BENZYL ALCOHOL; PETROLATUM; STEARYL ALCOHOL; PROPYLENE GLYCOL; ISOPROPYL MYRISTATE; POLYOXYL 40 STEARATE; CARBOMER HOMOPOLYMER TYPE B (ALLYL SUCROSE CROSSLINKED); SODIUM LAURYL SULFATE; EDETATE DISODIUM; SODIUM HYDROXIDE; WATER

Anusol-HC® 2.5%
(hydrocortisone cream, USP)

DESCRIPTION

The topical corticosteroids constitute a class of primarily synthetic steroids used as anti-inflammatory and antipruritic agents. Anusol-HC® 2.5% (hydrocortisone cream, USP) is a topical corticosteroid with hydrocortisone 2.5% (active ingredient) in a water-washable cream containing the following inactive ingredients: benzyl alcohol, petrolatum, stearyl alcohol, propylene glycol, isopropyl myristate, polyoxyl 40 stearate, carbomer homopolymer, sodium lauryl sulfate, edetate disodium, sodium hydroxide to adjust the pH, and purified water.

Hydrocortisone has the chemical name Pregn-4-ene-3,20-dione, 11,17, 21, trihydroxy-,(11β) - and the following chemical structure:

CLINICAL PHARMACOLOGY

Topical corticosteroids share anti-inflammatory, antipruritic and vasoconstrictive actions.

The mechanism of anti-inflammatory activity of the topical corticosteroids is unclear. Various laboratory methods, including vasoconstrictor assays, are used to compare and predict potencies and/or clinical efficacies of the topical corticosteroids. There is some evidence to suggest that a recognizable correlation exists between vasoconstrictor potency and therapeutic efficacy in man.

Pharmacokinetics:

The extent of percutaneous absorption of topical corticosteroids is determined by many factors including the vehicle, the integrity of the epidermal barrier, and the use of occlusive dressings.

Topical corticosteroids can be absorbed from normal intact skin. Inflammation and/or other disease processes in the skin increase percutaneous absorption. Occlusive dressings substantially increase the percutaneous absorption of topical corticosteroids. Thus, occlusive dressings may be a valuable therapeutic adjunct for treatment of resistant dermatoses (see DOSAGE AND ADMINISTRATION).

Once absorbed through the skin, topical corticosteroids are handled through pharmacokinetic pathways similar to systemically administered corticosteroids. Corticosteroids are bound to plasma proteins in varying degrees. Corticosteroids are metabolized primarily in the liver and are then excreted by the kidneys. Some of the topical corticosteroids and their metabolites are also excreted into the bile.

INDICATIONS AND USAGE

Topical corticosteroids are indicated for the relief of the inflammatory and pruritic manifestations of corticosteroid-responsive dermatoses.

CONTRAINDICATIONS

Topical corticosteroids are contraindicated in those patients with a history of hypersensitivity to any of the components of the preparation.

PRECAUTIONS

General:

Systemic absorption of topical corticosteroids has produced reversible hypothalamic-pituitary-adrenal (HPA) axis suppression, manifestations of Cushing’s syndrome, hyperglycemia, and glucosuria in some patients.

Conditions which augment systemic absorption include the application of the more potent steroids, use over large surface areas, prolonged use, and the addition of occlusive dressings.

If HPA axis suppression is noted (by using the urinary free cortisol and ACTH stimulation tests) an attempt should be made to withdraw the drug or to reduce the frequency of application.

Recovery of HPA axis function is generally prompt and complete upon discontinuation of the drug. Infrequently, signs and symptoms of steroid withdrawal may occur, requiring supplemental systemic corticosteroids.

Pediatric patients may absorb proportionally larger amounts of topical corticosteroids and thus be more susceptible to systemic toxicity (see PRECAUTIONS, Pediatric Use).

If irritation develops, topical corticosteroids should be discontinued and appropriate therapy instituted. In the presence of dermatological infections, the use of an appropriate antifungal or antibacterial agent should be instituted. If a favorable response does not occur promptly, the corticosteroid should be discontinued until the infection has been adequately controlled.

Information for the Patient:

Patients using topical corticosteroids should receive the following information and instructions:

1. This medication is to be used as directed by the physician. It is for external use only. Avoid contact with the eyes.
2. Patients should be advised not to use this medication for any disorder other than that for which it has been prescribed.
3. The treated skin area should not be bandaged or otherwise covered or wrapped as to be occlusive unless directed by the physician.
4. Patients should report any signs of local adverse reactions especially under occlusive dressing.
5. Parents of pediatric patients should be advised not to use tight-fitting diapers or plastic pants on a child being treated in the diaper area, as these garments may constitute occlusive dressings.

Laboratory Tests:

The urinary free cortisol test and the ACTH stimulation test may be helpful in evaluating the HPA axis suppression.

Carcinogenesis, Mutagenesis, and Impairment of Fertility:

Long-term animal studies have not been performed to evaluate the carcinogenic potential or the effect on fertility of topical corticosteroids. Studies to determine mutagenicity with hydrocortisone have revealed negative results.

Pregnancy:

Corticosteroids are generally teratogenic in laboratory animals when administered systemically at relatively low dosage levels. The more potent corticosteroids have been shown to be teratogenic after dermal application in laboratory animals. There are no adequate and well-controlled studies in pregnant women on teratogenic effects from topically applied corticosteroids.

Therefore, topical corticosteroids should be used during pregnancy only if the potential benefit justifies the potential risk to the fetus. Drugs of this class should not be used extensively on pregnant patients, in large amounts, or for prolonged periods of time.

Nursing Mothers:

It is not known whether topical administration of corticosteroids could result in sufficient systemic absorption to produce detectable quantities in breast milk. Systemically administered corticosteroids are secreted into breast milk in quantities not likely to have a deleterious effect on the infant. Nevertheless, caution should be exercised when topical corticosteroids are administered to a nursing woman.

Pediatric Use:

PEDIATRIC PATIENTS MAY DEMONSTRATE GREATER SUSCEPTIBILITY TO TOPICAL CORTICOSTEROID-INDUCED HPA AXIS SUPPRESSION AND CUSHING’S SYNDROME THAN MATURE PATIENTS BECAUSE OF A LARGER SKIN SURFACE AREA TO BODY WEIGHT RATIO.

Hypothalamic-pituitary-adrenal (HPA) axis suppression, Cushing’s syndrome, and intracranial hypertension have been reported in pediatric patients receiving topical corticosteroids. Manifestations of adrenal suppression in pediatric patients include linear growth retardation, delayed weight gain, low plasma cortisol levels, and absence of response to ACTH stimulation. Manifestations of intracranial hypertension include bulging fontanelles, headaches, and bilateral papilledema.

Administration of topical corticosteroids to pediatric patients should be limited to the least amount compatible with an effective therapeutic regimen. Chronic corticosteroid therapy may interfere with the growth and development of pediatric patients.

ADVERSE REACTIONS

The following local adverse reactions are reported infrequently with topical corticosteroids, but may occur more frequently with the use of occlusive dressings. These reactions are listed in an approximate decreasing order of occurrence:

Burning | Acneiform eruptions | Skin atrophy
Itching | Hypopigmentation | Striae
Irritation | Perioral dermatitis | Miliaria
Dryness | Allergic contact dermatitis
Folliculitis | Maceration of the skin
Hypertrichosis | Secondary infection

To report SUSPECTED ADVERSE REACTIONS, contact Salix Pharmaceuticals at 1-800-321-4576 or FDA at 1-800-FDA-1088 or www.fda.gov/medwatch.

OVERDOSAGE

Topically applied corticosteroids can be absorbed in sufficient amounts to produce systemic effects (see PRECAUTIONS).

DOSAGE AND ADMINISTRATION

Anusol-HC® 2.5% (hydrocortisone cream, USP) should be applied to the affected area two to four times daily depending on the severity of the condition.

Occlusive dressings may be used for the management of psoriasis or recalcitrant conditions. If an infection develops, the use of occlusive dressings should be discontinued and appropriate antimicrobial therapy instituted.

HOW SUPPLIED

Anusol-HC 2.5% (hydrocortisone cream, USP) is supplied as follows:
NDC 65649-401-30 30 g tube

Store at 20° to 25°C (68° to 77°F) [see USP Controlled Room Temperature]. PROTECT FROM FREEZING.

Distributed by:
  Salix Pharmaceuticals, a division
  of Bausch Health US, LLC
  Bridgewater, NJ 08807 USA
Anusol-HC is a registered trademark of Salix Pharmaceuticals, Inc. or its affiliates.
  © 2023 Salix Pharmaceuticals, Inc. or its affiliates

Manufactured by:
Padagis® US LLC
Minneapolis, MN 55427 USA
  Anusol-HC is a registered trademark of Salix Pharmaceuticals, Inc. or its affiliates.
  © 2023 Salix Pharmaceuticals, Inc. or its affiliates
Rev. 06/2023
9521003
2204609 7C800 9L PH4

PACKAGE LABEL PRINCIPAL DISPLAY PANEL –Carton 30 Grams

NDC 65649-401-30

Rx only

Anusol-HC® 2.5%

(hydrocortisone cream, USP)

For External Use Only
For Topical Use Only

Net Wt. 30 g

Salix
PHARMACEUTICALS